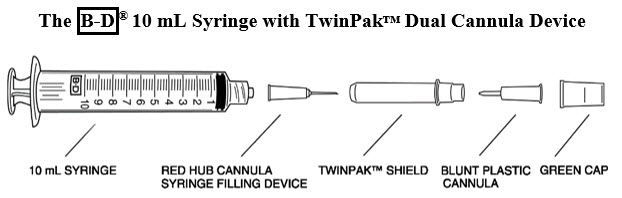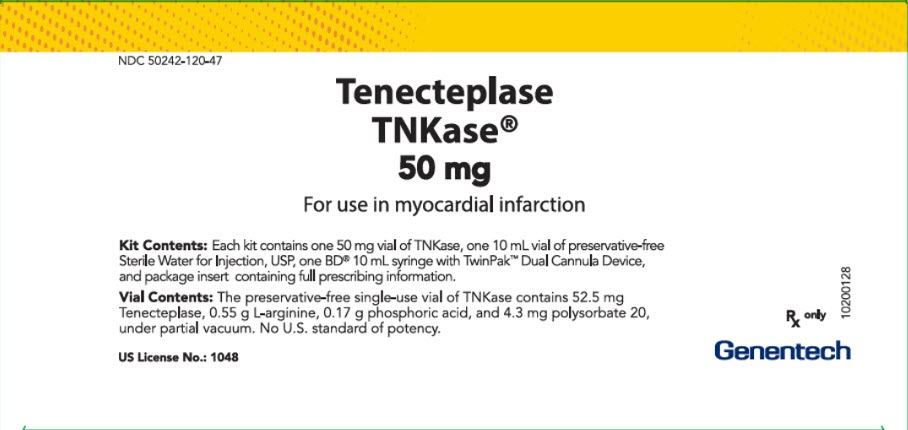 DRUG LABEL: TNKase
NDC: 50242-120 | Form: KIT | Route: INTRAVENOUS
Manufacturer: Genentech, Inc.
Category: prescription | Type: HUMAN PRESCRIPTION DRUG LABEL
Date: 20251215

ACTIVE INGREDIENTS: TENECTEPLASE 50 mg/10 mL
INACTIVE INGREDIENTS: ARGININE 522 mg/10 mL; PHOSPHORIC ACID 160 mg/10 mL; POLYSORBATE 20 4 mg/10 mL; WATER

HIGHLIGHTS OF PRESCRIBING INFORMATION

These highlights do not include all the information needed to use TNKASE safely and effectively. See full prescribing information for TNKASE.
TNKase® (tenecteplase) for injection, for intravenous use
Initial U.S. Approval: 2000

1 INDICATIONS AND USAGE

TNKase is a tissue plasminogen activator, indicated to reduce the risk of death associated with acute ST elevation myocardial infarction (STEMI). (1)

2 DOSAGE AND ADMINISTRATION

- Initiate treatment as soon as possible after the onset of STEMI symptoms. (2.1)
- TNKase is for intravenous administration only, administered as a single bolus over 5 seconds. Individualize dosage based on patient's weight. (2.1)

3 DOSAGE FORMS AND STRENGTHS

- For Injection: 50 mg as a white to pale yellow lyophilized powder in a single-dose vial for reconstitution with the co-packaged 10 mL Sterile Water for Injection USP (diluent). (3)

4 CONTRAINDICATIONS

- Active internal bleeding (4)
- History of cerebrovascular accident (4)
- Intracranial or intraspinal surgery or trauma within 2 months (4)
- Intracranial neoplasm, arteriovenous malformation, or aneurysm (4)
- Known bleeding diathesis (4)
- Severe uncontrolled hypertension (4)

5 WARNINGS AND PRECAUTIONS

- Bleeding: Increases the risk of bleeding. Avoid intramuscular injections. Monitor for bleeding. (5.1)
- Thromboembolism: The use of thrombolytics can increase the risk of thrombo-embolic events in patients with high likelihood of left heart thrombus. (5.2)
- Cholesterol Embolization: Has been reported in patients treated with thrombolytic agents. (5.3)
- Arrhythmias: It is recommended that anti-arrhythmic therapy for bradycardia and/or ventricular irritability be available when TNKase is administered. (5.4)
- Increased Risk of Heart Failure and Recurrent Ischemia when used with Planned Percutaneous Coronary Intervention (PCI) in STEMI: In patients with a large ST segment elevation myocardial infarction, physicians should choose either thrombolysis or PCI as the primary treatment strategy for reperfusion. Rescue PCI or subsequent elective PCI may be performed after administration of thrombolytic therapies if medically appropriate. (5.5)
- Hypersensitivity: Monitor patients treated with TNKase during and for several hours after infusion. If symptoms of hypersensitivity occur, initiate appropriate therapy (e.g., antihistamines, corticosteroids). (5.6)

6 ADVERSE REACTIONS

The most common adverse reactions are bleeding and hypersensitivity. (6)

To report SUSPECTED ADVERSE REACTIONS, contact Roche at 1-800-526-6367 or FDA at 1-800-FDA-1088 or www.fda.gov/medwatch.

7 DRUG INTERACTIONS

- During TNKase therapy, results of coagulation tests and/or measures of fibrinolytic activity may be unreliable unless specific precautions are taken to prevent in vitro artifacts. (7.1)

FULL PRESCRIBING INFORMATION

1 INDICATIONS AND USAGE

TNKase® is indicated to reduce the risk of death associated with acute ST elevation myocardial infarction (STEMI).

2 DOSAGE AND ADMINISTRATION

2.1 Recommended Dosage

Initiate treatment as soon as possible after the onset of STEMI symptoms.

TNKase is for intravenous (IV) administration only, administered as a single bolus over 5 seconds. Individualize dosage based on the patient's weight (see Table 1).

Table 1: Recommended Dosage
Patient Weight (kg) | TNKase (mg) | Volume TNKase [From one vial of TNKase reconstituted with 10 mL Sterile Water for Injection.] to be administered (mL)
< 60 | 30 | 6
≥ 60 to < 70 | 35 | 7
≥ 70 to < 80 | 40 | 8
≥ 80 to < 90 | 45 | 9
≥ 90 | 50 | 10

2.2 Preparation

Follow the below steps to prepare TNKase for administration:

Remove the shield assembly from the supplied B-D® 10 mL syringe with TwinPak™ Dual Cannula Device (see Figure 1) and aseptically withdraw 10 mL of Sterile Water for Injection, USP, from the supplied diluent vial using the red hub cannula syringe filling device. Only use the supplied Sterile Water for Injection, USP for reconstitution.

- Note: Do not discard the shield assembly.
- Aseptically reconstitute the vial with 10 mL Sterile Water for Injection, USP by directing the stream into the lyophilized powder to obtain a final concentration of 5 mg/mL. Slight foaming upon reconstitution is not unusual; any large bubbles will dissipate if the product is allowed to stand undisturbed for several minutes.
- Gently swirl until contents are completely dissolved. DO NOT SHAKE. The reconstituted preparation results in a colorless to pale yellow transparent solution.
- Determine the appropriate dose of TNKase [see Dosage and Administration (2.1)] and withdraw this volume (in milliliters) from the reconstituted vial with the syringe. Discard any unused solution.
- Stand the shield vertically on a flat surface (with green side down) and passively recap the red hub cannula.
- Remove the entire shield assembly, including the red hub cannula, by twisting counterclockwise. Note: The shield assembly also contains the clear-ended blunt plastic cannula; retain for split septum intravenous access.

Figure 1

2.3 Administration

Follow the below steps for administration of TNKase;

- Inspect the product prior to administration for particulate matter and discoloration. Administer TNKase as reconstituted at 5 mg/mL.
- Precipitation may occur when TNKase is administered in an intravenous line containing dextrose. Flush dextrose-containing lines with a saline-containing solution prior to and following single bolus administration of TNKase.
- Administer reconstituted TNKase as a single intravenous bolus over 5 seconds.
- Because TNKase contains no antibacterial preservatives, reconstitute immediately before use. If the reconstituted TNKase is not used immediately, refrigerate the TNKase vial at 2°C to 8°C (36°F to 46°F) and use within 8 hours.
- Although the supplied syringe is compatible with a conventional needle, this syringe is designed to be used with needleless intravenous systems. From the information below, follow the instructions applicable to the intravenous system in use.
  Split septum intravenous system: | - Remove the green cap. - Attach the clear-ended blunt plastic cannula to the syringe. - Remove the shield and use the blunt plastic cannula to access the split septum injection port. - Because the blunt plastic cannula has two side ports, air or fluid expelled through the cannula will exit in two sideways directions; direct away from face or mucous membranes.
  Luer-Lok® system: | Connect syringe directly to intravenous port.
  Conventional needle (not supplied in this kit): | Attach a large bore needle, e.g., 18 gauge, to the syringe's universal Luer-Lok®.
- Dispose of the syringe, cannula and shield per established procedures.

2.4 Chemical Incompatibilities

TNKase is incompatible with dextrose containing solutions. When used together, precipitation may occur. Flush dextrose containing lines with saline-containing solution before using TNKase.

3 DOSAGE FORMS AND STRENGTHS

For injection: 50 mg as a white to pale yellow lyophilized powder in a single-dose vial for reconstitution with the co-packaged 10 mL single-dose vial of Sterile Water for Injection, USP (diluent).

4 CONTRAINDICATIONS

TNKase is contraindicated in patients with [see Warnings and Precautions (5.1)]:

- Active internal bleeding
- History of cerebrovascular accident
- Intracranial or intraspinal surgery or trauma within 2 months
- Intracranial neoplasm, arteriovenous malformation, or aneurysm
- Known bleeding diathesis
- Severe uncontrolled hypertension

5 WARNINGS AND PRECAUTIONS

5.1 Bleeding

TNKase can cause bleeding, including intracranial hemorrhage and fatal bleeding. Concomitant use of other drugs that impair hemostasis increases the risk of bleeding.

Should serious bleeding that is not controlled by local pressure occur, discontinue any concomitant heparin or antiplatelet agents immediately and treat appropriately.

Avoid intramuscular injections and nonessential handling of the patient for the first few hours following treatment with TNKase. Perform arterial and venous punctures carefully and only as required. To minimize bleeding from noncompressible sites, avoid internal jugular and subclavian venous punctures. If an arterial puncture is necessary during TNKase infusion, use an upper extremity vessel that is accessible to manual compression. Apply pressure for at least 30 minutes.

5.2 Thromboembolism

The use of thrombolytics can increase the risk of thrombo-embolic events in patients with high likelihood of left heart thrombus, such as patients with mitral stenosis or atrial fibrillation.

5.3 Cholesterol Embolization

Cholesterol embolism has been reported in patients treated with thrombolytic agents. Investigate cause of any new embolic event and treat appropriately.

5.4 Arrhythmias

Coronary thrombolysis may result in arrhythmias associated with reperfusion. These arrhythmias (such as sinus bradycardia, accelerated idioventricular rhythm, ventricular premature depolarizations, ventricular tachycardia) may be managed with standard anti-arrhythmic measures. It is recommended that anti-arrhythmic therapy for bradycardia and/or ventricular irritability be available when TNKase is administered.

5.5 Increased Risk of Heart Failure and Recurrent Ischemia when used with Planned Percutaneous Coronary Intervention (PCI) in STEMI.

In a trial of patients with STEMI, there were trends toward worse outcomes in the individual components of the primary endpoint between TNKase plus PCI versus PCI alone (mortality 6.7% vs. 4.9%, respectively; cardiogenic shock 6.3% vs. 4.8%, respectively; and CHF 12% vs. 9.2%, respectively). In addition, there were trends towards worse outcomes in recurrent MI (6.1% vs. 3.7%, respectively; p = 0.03) and repeat target vessel revascularization (6.6% vs. 3.4%, respectively; p = 0.0045) in patients receiving TNKase plus PCI versus PCI alone [see Clinical Studies (14.1)]. In patients with large ST segment elevation myocardial infarction, physicians should choose either thrombolysis or PCI as the primary treatment strategy for reperfusion. Rescue PCI or subsequent elective PCI may be performed after administration of thrombolytic therapies if medically appropriate; however, the optimal use of adjunctive antithrombotic and antiplatelet therapies in this setting is unknown.

5.6 Hypersensitivity

Hypersensitivity, including urticarial / anaphylactic reactions, have been reported after administration of TNKase (e.g., anaphylaxis, angioedema, laryngeal edema, rash, and urticaria). Monitor patients treated with TNKase during and for several hours after infusion. If symptoms of hypersensitivity occur, initiate appropriate therapy (e.g., antihistamines, corticosteroids).

6 ADVERSE REACTIONS

The following adverse reactions are discussed in other sections of the label:

- Bleeding [see Contraindications (4), Warnings and Precautions (5.1)]
- Hypersensitivity [see Warnings and Precautions (5.6)]

6.1 Immunogenicity

Four of 625 (0.64%) patients tested for antibody formation to TNKase had a positive antibody titer at 30 days in studies with TNKase. The observed incidence of antibody positivity in an assay may be influenced by several factors including sample handling, concomitant medications, and underlying disease. For these reasons, comparison of the incidence of antibodies to TNKase with the incidence of antibodies to other products may be misleading.

7 DRUG INTERACTIONS

7.1 Drug/Laboratory Test Interactions

During TNKase therapy, results of coagulation tests and/or measures of fibrinolytic activity may be unreliable unless specific precautions are taken to prevent in vitro artifacts. Tenecteplase is an enzyme that, when present in blood in pharmacologic concentrations, remains active under in vitro conditions. This can lead to degradation of fibrinogen in blood samples removed for analysis.

8 USE IN SPECIFIC POPULATIONS

8.1 Pregnancy

Risk Summary

There are risks to the mother and fetus from acute ST elevation myocardial infarction, which is a medical emergency in pregnancy and can be fatal if left untreated (see Clinical Considerations). Published data consisting of a small number of case reports involving the use of related thrombolytic agents in pregnant women have not identified an increased risk of major birth defects. There are no data on the use of tenecteplase during pregnancy to evaluate for a drug-associated risk of major birth defects, miscarriage, or adverse maternal or fetal outcomes.

TNKase does not elicit maternal and direct embryo toxicity in rabbits following a single IV administration. In developmental toxicity studies conducted in rabbits, the no observable effect level (NOEL) of a single IV administration of TNKase on maternal or developmental toxicity (5 mg/kg) was approximately 7 times human exposure (based on AUC) at the dose for STEMI.

The estimated background risk of major birth defects and miscarriage for the indicated population is unknown. All pregnancies have a background risk of birth defect, loss, or other adverse outcomes. In the U.S. general population, the estimated background risk of major birth defects and miscarriage in clinically recognized pregnancies is 2% to 4% and 15% to 20%, respectively.

Clinical Considerations

Disease-Associated Maternal and/or Embryo/Fetal Risk

Myocardial infarction is a medical emergency which can be fatal if left untreated. Life-sustaining therapy for the pregnant woman should not be withheld because of potential concerns regarding the effects of tenecteplase on the fetus.

8.2 Lactation

Risk Summary

There are no data on the presence of tenecteplase in either human or animal milk, the effects on the breastfed infant, or the effect on milk production. The developmental and health benefits of breastfeeding should be considered along with the mother's clinical need for TNKase and any potential adverse effects on the breastfed infant from the TNKase or from the underlying maternal condition.

8.4 Pediatric Use

The safety and effectiveness of TNKase in pediatric patients have not been established.

8.5 Geriatric Use

In the ASSENT-2 study, 41% (3500/8458) of patients who were treated with TNKase were aged 65 years or older. In this population, rates of 30-day mortality, stroke, intracranial hemorrhage and major bleeds requiring blood transfusion or leading to hemodynamic complications were higher than in those aged less than 65 years.

11 DESCRIPTION

Tenecteplase is a tissue plasminogen activator (tPA) produced by recombinant DNA technology using a mammalian cell line (Chinese Hamster Ovary cells). Tenecteplase is a 527-amino acid glycoprotein developed by introducing the following modifications to the complementary DNA (cDNA) for natural human tPA: a substitution of threonine 103 with asparagine, and a substitution of asparagine 117 with glutamine, both within the kringle 1 domain, and a tetra-alanine substitution at amino acids 296–299 in the protease domain. It has a molecular weight of 58,742 daltons. Biological potency is determined by an in vitro clot lysis assay and is expressed in tenecteplase specific units. The specific activity of tenecteplase has been defined as 200 units/mg.

TNKase (tenecteplase) for injection is a sterile, white to pale yellow, lyophilized powder for intravenous bolus administration after reconstitution with Sterile Water for Injection, USP. Each single-dose vial of TNKase nominally contains 50 mg of tenecteplase, arginine (522 mg), phosphoric acid (approximately 160 mg), and polysorbate 20 (4.0 mg). Following reconstitution with the supplied 10 mL single-dose vial of Sterile Water for Injection, USP, the final concentration is 5 mg/mL with a pH of approximately 7.3.

12 CLINICAL PHARMACOLOGY

12.1 Mechanism of Action

Tenecteplase is a modified form of human tissue plasminogen activator (tPA) that binds to fibrin and converts plasminogen to plasmin. In the presence of fibrin, in vitro studies demonstrate that tenecteplase-mediated conversion of plasminogen to plasmin is increased relative to its conversion in the absence of fibrin. This fibrin specificity decreases systemic activation of plasminogen and the resulting degradation of circulating fibrinogen as compared to a molecule lacking this property. The clinical significance of fibrin-specificity on safety (e.g., bleeding) or efficacy has not been established.

12.2 Pharmacodynamics

Following administration of 30, 40, or 50 mg of TNKase, there are decreases in circulating fibrinogen (4%–15%) and plasminogen (11%–24%).

12.3 Pharmacokinetics

Distribution

In patients with STEMI, TNKase administered as a single IV bolus exhibits a biphasic disposition from the plasma.

Volume of distribution at central compartment ranges from 4.22 to 5.43 L, approximating plasma volume. Steady-state volume of distribution was approximately 50% greater (6.12 to 8.01 L), suggestive of some extravascular distribution.

Elimination

After IV bolus administration, the terminal phase half-life of tenecteplase was 90 to 130 minutes. In 99 of 104 patients treated with TNKase, TNKase has linear PK with mean maximum concentrations increased in a dose-proportional manner and mean plasma clearance was similar for the 30, 40, and 50 mg doses ranging from 99 to 119 mL/min.

Metabolism

Liver metabolism is the major clearance mechanism for tenecteplase.

Body weight

A stepwise linear regression analysis indicated that total body weight explained 19% of the variability in plasma clearance and 11% of the variability in volume of distribution.

13 NONCLINICAL TOXICOLOGY

13.1 Carcinogenesis, Mutagenesis, Impairment of Fertility

Studies in animals have not been performed to evaluate the carcinogenic potential, mutagenicity, or the effect on fertility.

14 CLINICAL STUDIES

14.1 Acute Myocardial Infarction

ASSENT-2

The Assessment of the Safety and Efficacy of a New Thrombolytic (ASSENT-2) study was an international, randomized, double-blind trial that compared 30-day mortality rates in 16,949 patients assigned to receive an IV bolus dose of TNKase or an accelerated infusion of Activase® (alteplase). Eligibility criteria included onset of chest pain within 6 hours of randomization and ST-segment elevation or left bundle branch block on electrocardiogram (ECG). Patients were to be excluded from the trial if they received GP IIb/IIIa inhibitors within the previous 12 hours. TNKase was dosed using actual or estimated weight in a weight-tiered fashion as described in Dosage and Administration (2.1). All patients were to receive 150–325 mg of aspirin administered as soon as possible, followed by 150–325 mg daily. Intravenous heparin was to be administered as soon as possible: for patients weighing ≤ 67 kg, heparin was administered as a 4000-unit IV bolus followed by infusion at 800 U/hr; for patients weighing > 67 kg, heparin was administered as a 5000-unit IV bolus followed by infusion at 1000 U/hr. Heparin was continued for 48 to 72 hours with infusion adjusted to maintain aPTT at 50–75 seconds. The use of GP IIb/IIIa inhibitors was discouraged for the first 24 hours following randomization. The results of the primary endpoint (30-day mortality rates with non-parametric adjustment for the covariates of age, Killip class, heart rate, systolic blood pressure and infarct location) along with selected other 30-day endpoints are shown in Table 2.

Table 2 ASSENT-2 Mortality, Stroke, and Combined Outcome of Death or Stroke Measured at Thirty Days
30-Day Events | TNKase (n = 8461) | Accelerated Activase (n = 8488) | Relative Risk TNKase/Activase (95% CI)
Mortality | 6.2% | 6.2% | 1.00 (0.89, 1.12)
Intracranial Hemorrhage (ICH) | 0.9% | 0.9% | 0.99 (0.73, 1.35)
Any Stroke | 1.8% | 1.7% | 1.07 (0.86, 1.35)
Death or Nonfatal Stroke | 7.1% | 7.0% | 1.01 (0.91, 1.13)

Rates of mortality and the combined endpoint of death or stroke among pre-specified subgroups, including age, gender, time to treatment, infarct location, and history of previous myocardial infarction, demonstrate consistent relative risks across these subgroups. There was insufficient enrollment of non-Caucasian patients to draw any conclusions regarding relative efficacy in racial subsets.

Rates of in-hospital procedures, including percutaneous transluminal coronary angioplasty (PTCA), stent placement, intra-aortic balloon pump (IABP) use, and coronary artery bypass graft (CABG) surgery, were similar between the TNKase and Activase (alteplase) groups.

TIMI-10B

TIMI 10B was an open-label, controlled, randomized, dose-ranging, angiography study which utilized a blinded core laboratory for review of coronary arteriograms. Patients (n = 837) presenting within 12 hours of symptom onset were treated with fixed doses of 30, 40, or 50 mg of TNKase or the accelerated infusion of Activase and underwent coronary arteriography at 90 minutes. The primary endpoint was the rate of TIMI Grade 3 flow at 90 minutes. The results showed that the 40 mg and 50 mg doses were similar to accelerated infusion of Activase in restoring patency. TIMI Grade 3 flow and TIMI Grade 2/3 flow at 90 minutes are shown in Table 3. The exact relationship between coronary artery patency and clinical activity has not been established.

Table 3 TIMI 10B Patency Rates TIMI Grade Flow at 90 Minutes
 | Activase ≤100 mg (n=311) | TNKase 30 mg (n=302) | TNKase 40 mg (n=148) | TNKase 50 mg (n=76)
TIMI Grade 3 Flow | 62.7% | 54.3% | 62.8% | 65.8%
(95% CI) | (57.1%, 68.1%) | (48.5%, 60.0%) | (54.5%, 70.6%) | (54.0%, 76.3%)
TIMI Grade 2/3 Flow | 81.7% | 76.8% | 79.1% | 88.2%
(95% CI) | (76.9%, 85.8%) | (71.6%, 81.5%) | (71.6%, 85.3%) | (78.7%, 94.4%)

The angiographic results from TIMI 10B and the safety data from ASSENT-1, an additional uncontrolled safety study of 3,235 TNKase-treated patients, provided the framework to develop a weight-tiered TNKase dose regimen. Exploratory analyses suggested that a weight-adjusted dose of 0.5 to 0.6 mg/kg of TNKase resulted in a better patency to bleeding relationship than fixed doses of TNKase across a broad range of patient weights.

ASSENT 4 PCI

The Assessment of the Safety and Efficacy of a New Treatment Strategy with Percutaneous Coronary Intervention (ASSENT 4 PCI) was a phase IIIb/IV study designed to assess the safety and effectiveness of a strategy of administering full dose TNKase with a single bolus of 4000 U of unfractionated heparin in patients with STEMI, in whom primary percutaneous coronary intervention (PCI) was planned, but in whom a delay of 1-3 hours was anticipated before PCI. The trial was prematurely terminated with 1667 randomized patients (75 of whom were in the United States) due to a numerically higher mortality in the patients receiving TNKase prior to primary PCI versus PCI without TNKase (median time from randomization to balloon was 115 minutes in patients who were treated with TNKase plus PCI versus 107 minutes in patients who were treated with PCI alone). The incidence of the 90-day primary endpoint, a composite of death or cardiogenic shock or congestive heart failure (CHF) within 90 days, was 18.6% in patients treated with TNKase plus PCI versus 13.4% in those treated with PCI alone (p = 0.0045; RR 1.39 (95% CI 1.11–1.74)).

There were trends toward worse outcomes in the individual components of the primary endpoint between TNKase plus PCI versus PCI alone (mortality 6.7% vs. 4.9%, respectively; cardiogenic shock 6.3% vs. 4.8%, respectively; and CHF 12.0% vs. 9.2%, respectively). In addition, there were trends towards worse outcomes in recurrent MI (6.1% vs. 3.7%, respectively; p = 0.03) and repeat target vessel revascularization (6.6% vs. 3.4%, respectively; p = 0.004) in patients receiving TNKase plus PCI versus PCI alone [see Warnings and Precautions (5.5)].

There was no difference in in-hospital major bleeding between the two groups (5.6% vs. 4.4% for TNKase plus PCI vs. PCI alone, respectively). For patients treated with TNKase plus PCI, in-hospital rates of intracranial hemorrhage and total stroke were similar to those observed in previous trials (0.97% and 1.8%, respectively); however, none of the patients treated with PCI alone experienced a stroke (ischemic, hemorrhagic or other).

16 HOW SUPPLIED/STORAGE AND HANDLING

16.1 How Supplied

TNKase (tenecteplase) for injection is supplied as a sterile, white to pale yellow lyophilized powder in a 50 mg single-dose vial under partial vacuum.

Each 50 mg single-dose vial of TNKase is packaged with one 10 mL single-dose vial of Sterile Water for Injection, USP for reconstitution, and the B-D® 10 mL syringe with TwinPak™ Dual Cannula Device: NDC 50242-120-47.

16.2 Stability and Storage

Store lyophilized TNKase at room temperature up to 30°C (86°F) or refrigerated at 2°C to 8°C (36°F to 46°F). Do not use beyond the expiration date stamped on the vial.

TNKase® (tenecteplase)

Manufactured by:
Genentech, Inc.

A Member of the Roche Group
1 DNA Way
South San Francisco, CA
94080-4990

U.S. License No. 1048

TNKase® is a registered trademark of Genentech, Inc.

©2023 Genentech, Inc.

PRINCIPAL DISPLAY PANEL - Kit Carton

NDC 50242-120-47

Tenecteplase
TNKase®
50 mg

For use in myocardial infarction

Kit Contents: Each kit contains one 50 mg vial of TNKase, one 10 mL vial of preservative-free
Sterile Water for Injection, USP, one BD® 10 mL syringe with TwinPak™ Dual Cannula Device,
and package insert containing full prescribing information.

Vial Contents: The preservative-free single-use vial of TNKase contains 52.5 mg
Tenecteplase, 0.55 g L-arginine, 0.17 g phosphoric acid, and 4.3 mg polysorbate 20,
under partial vacuum. No U.S. standard of potency.

Rx only

US License No.: 1048

Genentech

10200128